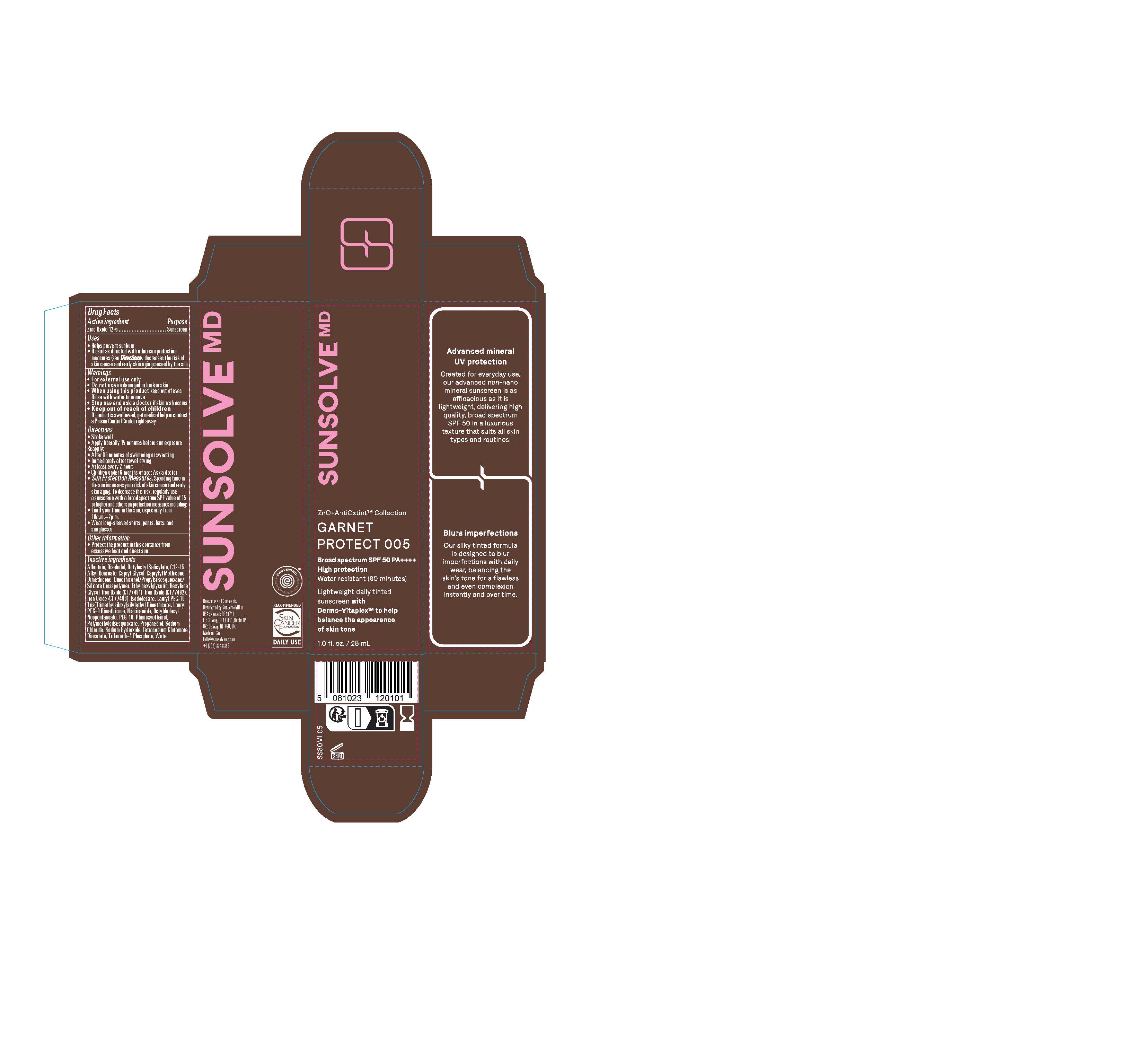 DRUG LABEL: Sunsolve MD Mineral Shade Garnet 005
NDC: 84878-405 | Form: LOTION
Manufacturer: Sunsolve MD Inc
Category: otc | Type: HUMAN OTC DRUG LABEL
Date: 20251114

ACTIVE INGREDIENTS: ZINC OXIDE 132 mg/1 mL
INACTIVE INGREDIENTS: TRIETHOXYCAPRYLYLSILANE; TRILAURETH-4 PHOSPHATE; BUTYLOCTYL SALICYLATE; OCTYLDODECYL NEOPENTANOATE; ISODODECANE; .ALPHA.-BISABOLOL, (+)-; WATER; NIACINAMIDE; ETHYLHEXYLGLYCERIN; HEXYLENE GLYCOL; DIMETHICONOL/PROPYLSILSESQUIOXANE/SILICATE CROSSPOLYMER (450000000 MW); PROPANEDIOL; TETRASODIUM GLUTAMATE DIACETATE; SODIUM CHLORIDE; PHENOXYETHANOL; ALLANTOIN; POLYMETHYLSILSESQUIOXANE (4.5 MICRONS); FERRIC OXIDE RED; ALKYL (C12-15) BENZOATE; CAPRYLYL METHICONE; DIMETHICONE; FERROSOFERRIC OXIDE; LAURYL PEG-8 DIMETHICONE (300 CPS); FERRIC OXIDE YELLOW

Sunsolve MD Mineral Shade Garnet 005